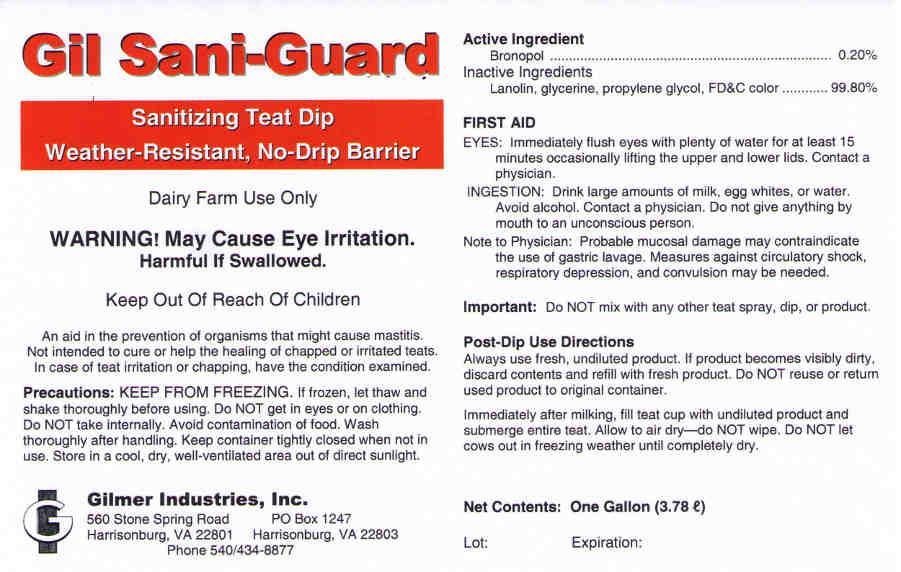 DRUG LABEL: Gil Sani-Guard
NDC: 54420-008 | Form: LIQUID
Manufacturer: Gilmer Industries, Inc.
Category: animal | Type: OTC ANIMAL DRUG LABEL
Date: 20130227

ACTIVE INGREDIENTS: BRONOPOL 2000 mg/1 L

Gil Sani-Guard

PURPOSE

Sanitizing Teat Dip
Weather-Resistant, No-Drip Barrier

Dairy Farm Use Only

WARNING! May Cause Eye Irritation.
Harmful If Swallowed.

Keep Out Of Reach Of Children

An aid in the prevention of organisms that might cause mastitis.
Not intended to cure or help the healing of chapped or irritated teats.
In case of teat irritation or chapping, have the condition examined.

Precautions:
KEEP FROM FREEZING.
If frozen, let thaw and shake thoroughly before using.
Do NOT get in eyes or on clothing.
Do NOT take internally.
Do NOT allow to contaminate food.
Wash thoroughly after handling.
Keep container tightly closed when not in use.
Store in a cool, dry, well-ventilated area out of direct sunlight.

Active Ingredient

Bronopol.................................................................... 0.20%

Inactive Ingredients

Lanolin, glycerine, propylene glycol, FD&C color .......... 99.80%

USER SAFETY WARNINGS

FIRST AID

EYES: Immediately flush eyes wtih plenty of water for at least 15 minutes occassionally lifting the upper and lower lids. Contact a physician.

INGESTION: Drink large amounts of milk, egg whites, or water. Avoid alcohol. Contact a physician. Do not give anything by mouth to an unconscious person.

Note to Physician: Probable mucosal damage may contraindicate the use of gastric lavage. Measures against circulatory shock, respiratory depression, and convulsion may be needed.

DOSAGE AND ADMINISTRATION

Important: Do NOT mix with any other teat spray, dip, or product.

Post-Dip Use Directions

Always use fresh, undiluted product.
If product becomes visibly dirty, discard contents and refill with fresh product.
Do NOT reuse or return used product to original container.

Immediately after milking, fill teat cup iwth undiluted product and submerge entire teat.
Allow to air dry--do NOT wipe.
Do NOT let cows out in freezing weather until completely dry.